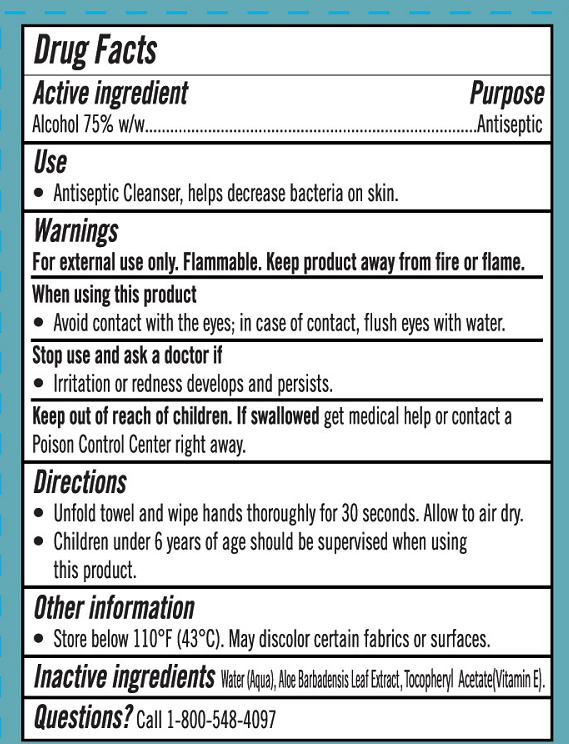 DRUG LABEL: Wet Wipes
NDC: 78936-004 | Form: SWAB
Manufacturer: Hangzhou Caring Cleaning Commodity Co.,Ltd
Category: otc | Type: HUMAN OTC DRUG LABEL
Date: 20200623

ACTIVE INGREDIENTS: ALCOHOL 75 g/100 g
INACTIVE INGREDIENTS: ALOE VERA LEAF; WATER; ALPHA-TOCOPHEROL ACETATE

Wet Wipes

Active Ingredient(s)

Alcohol 75 g/100g w/w....Antiseptic

Purpose

Antiseptic

Use

Antiseptic Cleanser, helps decrease bacteria on skin.

Warnings

For external use only. Flammable, keep product away from fire or flame.

When using this product, avoid contact with the eyes; in case of contact, flush eyes with water.

Stop use and ask a doctor if irritation or redness develops and persists.

Keep out of reach of children. If swallowed, get medical help or contact a Poison Control Center right away.

Inactive ingredients

Water(Aqua),Aloe Barbadensis Leaf Extract, Tocopheryl Acetate(Vitamin E)

Directions

Unfold towel and wipe hands thoroughly for 30 seconds. Allow to air dry.

Children under 6 years of age should be supervised when using this product.

Other information

Store below 110°F (43℃). May discolor certain fabrics or surfaces.

Package Label - Principal Display Panel

1 PC IN 1 PACKAGE NDC: 78936-004-01